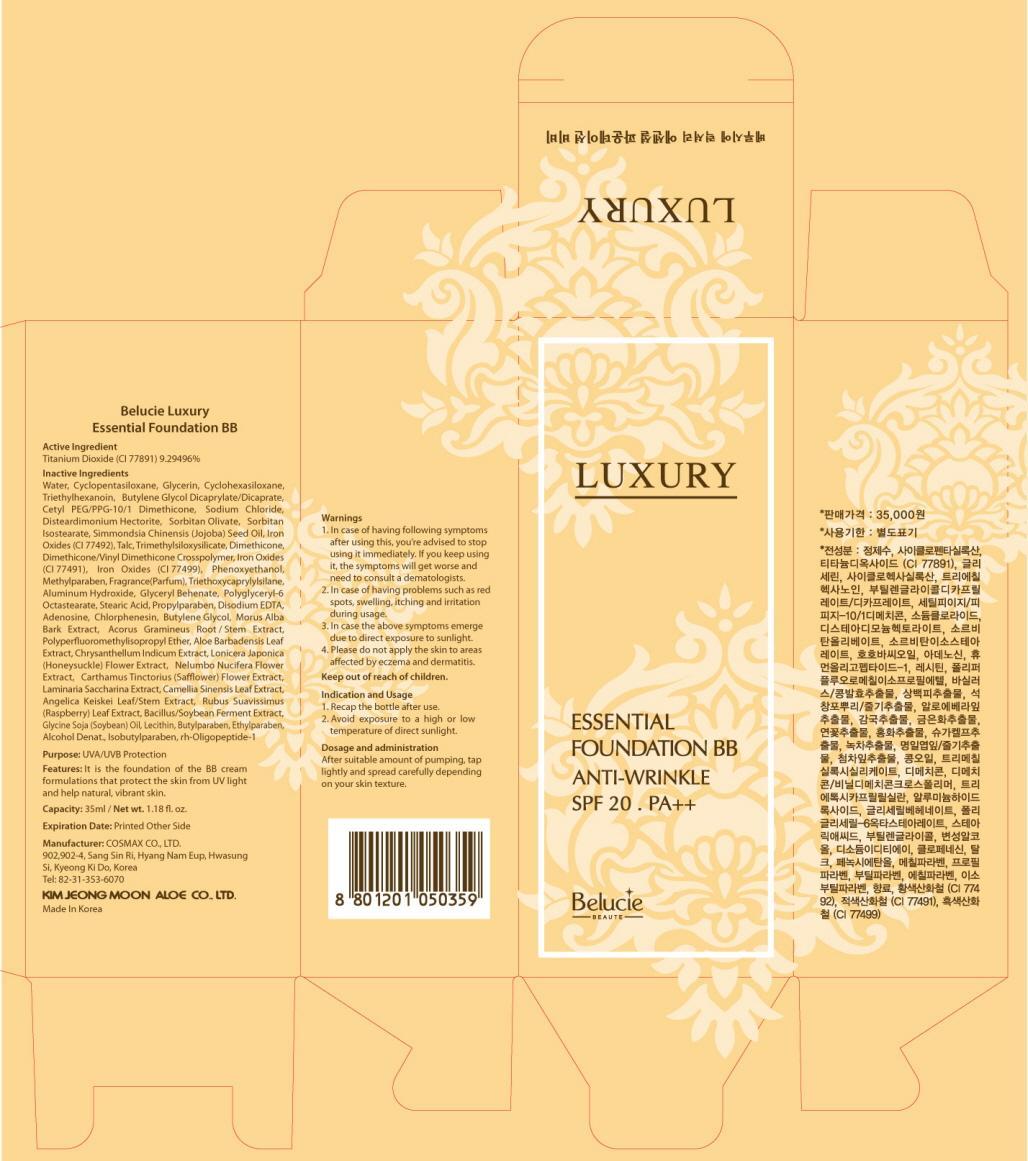 DRUG LABEL: Belucie Luxury Essential foundation BB
NDC: 50410-030 | Form: CREAM
Manufacturer: KIMJEONGMOON ALOE CO., LTD.
Category: otc | Type: HUMAN OTC DRUG LABEL
Date: 20121129

ACTIVE INGREDIENTS: Titanium Dioxide 3.25 g/35 mL
INACTIVE INGREDIENTS: Water; Glycerin; Triethylhexanoin; Butylene Glycol

ACTIVE INGREDIENT

Active Ingredient: Titanium Dioxide (CI 77891) 9.29496%

INACTIVE INGREDIENT

Inactive Ingredients : Water, Cyclopentasiloxane, Glycerin, Cyclohexasiloxane, Triethylhexanoin, Butylene Glycol Dicaprylate/Dicaprate, Cetyl PEG/PPG-10/1 Dimethicone, Sodium Chloride, Disteardimonium Hectorite, Sorbitan Olivate, Sorbitan Isostearate, Simmondsia Chinensis (Jojoba) Seed Oil, Iron Oxides (CI 77492), Talc, Trimethylsiloxysilicate, Dimethicone, Dimethicone/Vinyl Dimethicone Crosspolymer, Iron Oxides (CI 77491), Iron Oxides (CI 77499), Phenoxyethanol, Methylparaben ,Fragrance(Parfum), Triethoxycaprylylsilane, Aluminum Hydroxide, Glyceryl Behenate, Polyglyceryl-6 Octastearate, Stearic Acid, Propylparaben, Disodium EDTA, Adenosine, Chlorphenesin, Butylene Glycol, Morus Alba Bark Extract, Acorus Gramineus Root/Stem Extract, Polyperfluoromethylisopropyl Ether, Aloe Barbadensis Leaf Extract, Chrysanthellum Indicum Extract, Lonicera Japonica (Honeysuckle) Flower Extract, Nelumbo Nucifera Flower Extract, Carthamus Tinctorius (Safflower) Flower Extract, Laminaria Saccharina Extract, Camellia Sinensis Leaf Extract, Angelica Keiskei Leaf/Stem Extract, Rubus Suavissimus (Raspberry) Leaf Extract, Bacillus/Soybean Ferment Extract, Glycine Soja (Soybean) Oil, Lecithin, Butylparaben, Ethylparaben, Alcohol Denat., Isobutylparaben, rh-Oligopeptide-1

PURPOSE

Purpose: UVA/UVB Protection

WARNINGS

1. In case of having following symptoms after using this, you’re advised to stop using it immediately. If you keep using it, the symptoms will get worse and need to consult a dematologists.
2. In case of having problems such as red spots, swelling, itching and irritation during usage
3. In case the above symptoms emerge due to direct exposure to sunlight
4. Please do not apply the skin to areas affected by eczema and dermatitis

KEEP OUT OF REACH OF CHILDREN

INDICATIONS AND USAGE

Indication and usage
1. Recap the bottle after use.
2. Avoid exposure to a high or low temperature of direct sunlight

DOSAGE AND ADMINISTRATION

After suitable amount of pumping, tap lightly and spread carefully depending on your skin texture.